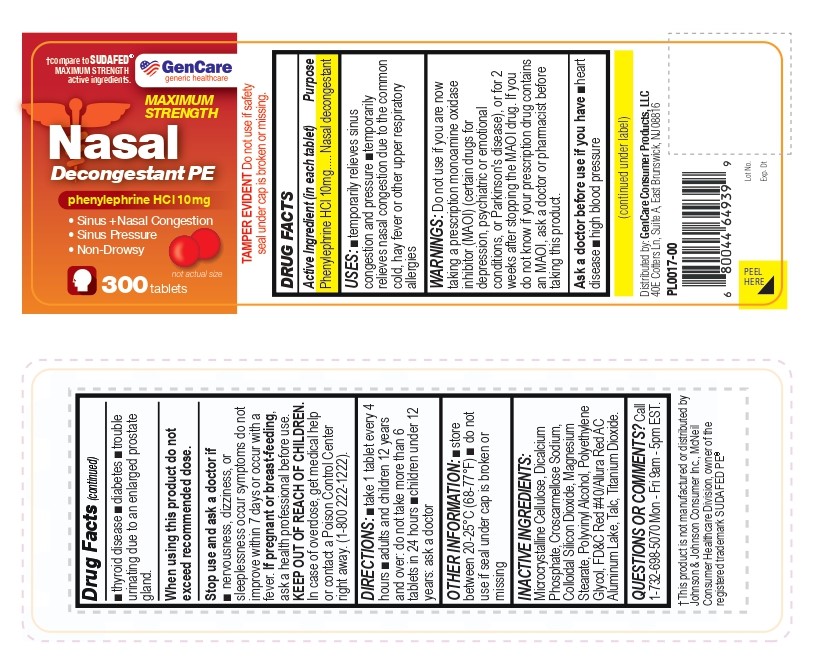 DRUG LABEL: Gencare-Nasal Decongestant PE
NDC: 72090-025 | Form: TABLET
Manufacturer: Pioneer Life Sciences, LLC
Category: otc | Type: HUMAN OTC DRUG LABEL
Date: 20251226

ACTIVE INGREDIENTS: PHENYLEPHRINE HYDROCHLORIDE 10 mg/1 1
INACTIVE INGREDIENTS: MICROCRYSTALLINE CELLULOSE; DICALCIUM PHOSPHATE; CROSCARMELLOSE SODIUM; SILICON DIOXIDE; MAGNESIUM STEARATE; POLYVINYL ALCOHOL; POLYETHYLENE GLYCOL, UNSPECIFIED; FD&C RED NO. 40 ALUMINUM LAKE; TALC; TITANIUM DIOXIDE

Gencare-Nasal Decongestant PE

Active Ingredient (in each tablet)

Phenylephrine HCl 10mg

Purpose

Nasal decongestant

USES:

- temporarily relieves sinus congestion and pressure
- temporarily relieves nasal congestion due to the common cold, hay fever or other upper respiratory allergies

WARNINGS

Do not use if you are now taking a prescription monoamine oxidase inhibitor (MAOI) (certain drugs for depression, psychiatric or emotional conditions, or Parkinson's disease), or for 2 weeks after stopping the MAOI drug. If you do not know if your prescription drug contains an MAOI, ask a doctor or pharmacist before taking this product.

Ask a doctor before use if you have

- heart disease
- high blood pressure
- thyroid disease
- diabetes
- trouble urinating due to an enlarged prostate gland.

When using this product do not exceed recommended dose.

Stop use and ask a doctor if

- nervousness, dizziness, or sleeplessness occur symptoms do not improve within 7 days or occur with a fever.

PREGNANCY OR BREAST FEEDING

If pregnant or breast-feeding, ask a health professional before use.

KEEP OUT OF REACH OF CHILDREN. In case of overdose, get medical help or contact a Poison Control Center right away. (1-800 222-1222).

DIRECTIONS:

- take 1 tablet every 4 hours
- adults and children 12 years and over: do not take more than 6 tablets in 24 hours
- children under 12 years: ask a doctor

OTHER INFORMATION

- store between 20-25°C (68-77°F)
- do not use if seal under cap is broken or missing

INACTIVE INGREDIENTS

Microcrystalline Cellulose, Dicalcium Phosphate, Croscarmellose Sodium, Colloidal Silicon Dioxide, Magnesium Stearate, Polyvinyl Alcohol, Polyethylene Glycol, FD&C Red #40/Allura Red AC Aluminum Lake, Talc, Titanium Dioxide.

QUESTIONS OR COMMENTS?

Call 1-732-698-5070 Mon - Fri 9am - 5pm EST.